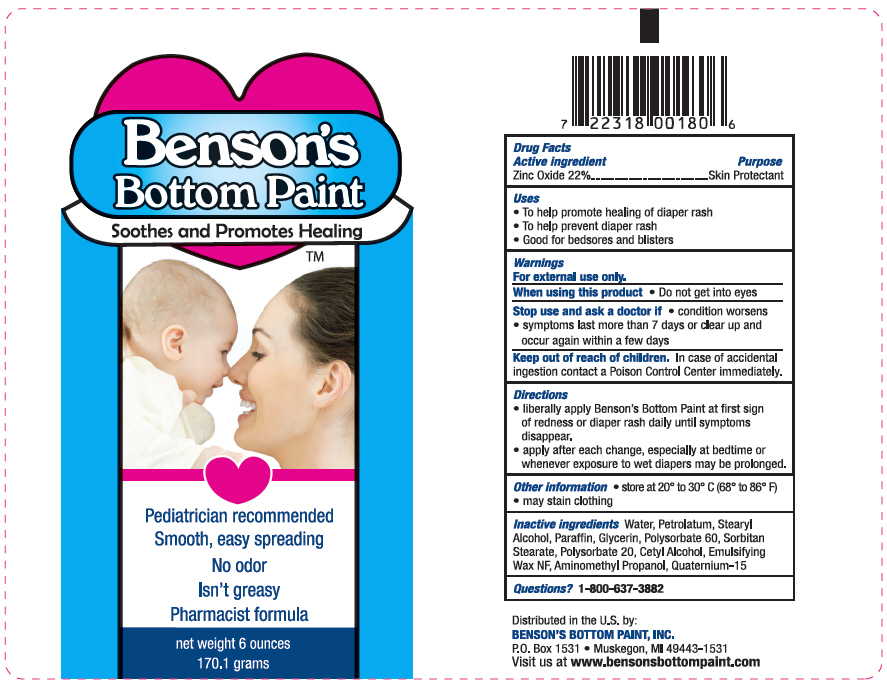 DRUG LABEL: Benson Bottom Paint
NDC: 71706-060 | Form: CREAM
Manufacturer: Benson's Bottom Paint , Inc
Category: otc | Type: HUMAN OTC DRUG LABEL
Date: 20200108

ACTIVE INGREDIENTS: Zinc Oxide 220 mg/1 g
INACTIVE INGREDIENTS: Water; Glycerin; Aminomethylpropanol; Polysorbate 20; Petrolatum; Stearyl Alcohol; Cetyl Alcohol; Paraffin; Sorbitan Monostearate; Polysorbate 60; Polawax Polysorbate; Quaternium-15 CIS-Form

Benson Bottom Paint

Drug Facts

Active Ingredient

Zinc Oxide 22%

Purpose

Skin Protectant

Uses

- To help promote healing of diaper rash
- To help prevent diaper rash
- Good for bedsores and blisters

Warnings

For external use only

When using this product

- Do not get into eyes

Stop use and ask a doctor if

- Condition worsens
- Symptoms last more than 7 days or clear up and occur again within a few days

Keep out of reach of children. In case of accidental ingestion contact a Poison Control Center immediately.

Directions

- liberally apply Benson's Bottom Paint at first sign of redness or diaper rash daily until symptoms disappear.
- apply after each change, especially at bedtime or whenever exposure to wet diapers may be prolonged

Other information

- store at 20° to 30 ° C (68-86 °F)
- may stain clothing

Inactive Ingredients

Water, Petrolatum, Stearyl Alcohol, Paraffin, Glycerin, Polysorbate 60, Sorbitan steareate, Polysorbate 20, Cetyl Alcohol, Emulsifying Wax, NF, Aminomethyl Propanol, Quaternium-15

Questions?

1-800-637-3882

Distributed in the U.S. by:
BENSON'S BOTTOM PAINT, INC.
P.O. Box 1531 • Muskegon, MI 49443-1531

PRINCIPAL DISPLAY PANEL - 170.1 gram Tube Label

Benson's
Bottom Paint

Soothes and Promotes Healing
™

Pediatrician recommended
Smooth, easy spreading
No odor
Isn't greasy
Pharmacist formula

net weight 6 ounces
170.1 grams